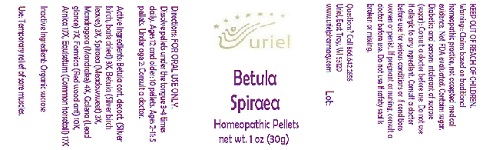 DRUG LABEL: Betula Spiraea
NDC: 48951-2069 | Form: PELLET
Manufacturer: Uriel Pharmacy Inc.
Category: homeopathic | Type: HUMAN OTC DRUG LABEL
Date: 20180531

ACTIVE INGREDIENTS: BETULA PUBESCENS BARK 3 [hp_X]/1 1; BETULA PUBESCENS LEAF 3 [hp_X]/1 1; FILIPENDULA ULMARIA ROOT 3 [hp_X]/1 1; MANDRAGORA OFFICINARUM ROOT 4 [hp_X]/1 1; LEAD SULFIDE 7 [hp_X]/1 1; FORMICA RUFA 10 [hp_X]/1 1; ARNICA MONTANA 17 [hp_X]/1 1; EQUISETUM ARVENSE TOP 17 [hp_X]/1 1
INACTIVE INGREDIENTS: SUCROSE

Betula Spiraea

INDICATIONS AND USAGE

Directions: FOR ORAL USE ONLY.

DOSAGE AND ADMINISTRATION

Dissolve pellets under the tongue 3-4 times daily. Ages 12 and older: 10 pellets. Ages 2-11: 5 pellets. Under age 2: Consult a doctor.

ACTIVE INGREDIENT

Active Ingredients: Betula cort. decoct. (Silver birch, bark dried) 3X, Betula (Silver birch leaves) 3X, Spiraea (Meadowsweet) 3X, Mandragora (Mandrake) 4X, Galena (Lead glance) 7X, Formica (Red wood ant) 10X, Arnica 17X, Equisetum (Common horsetail) 17X

Inactive Ingredient: Organic sucrose

PURPOSE

Use: Temporary relief of sore muscles.

KEEP OUT OF REACH OF CHILDREN.

WARNINGS

Warnings: Claims based on traditional homeopathic practice, not accepted medical evidence. Not FDA evaluated. Contains sugar. Diabetics and persons intolerant of sucrose (sugar): Consult a doctor before use. Do not use if allergic to any ingredient. Consult a doctor before use for serious conditions or if conditions worsen or persist. If pregnant or nursing, consult a doctor before use. Do not use if safety seal is broken or missing.

QUESTIONS

Questions? Call 866.642.2858 Uriel, East Troy, WI 53120 www.urielpharmacy.com